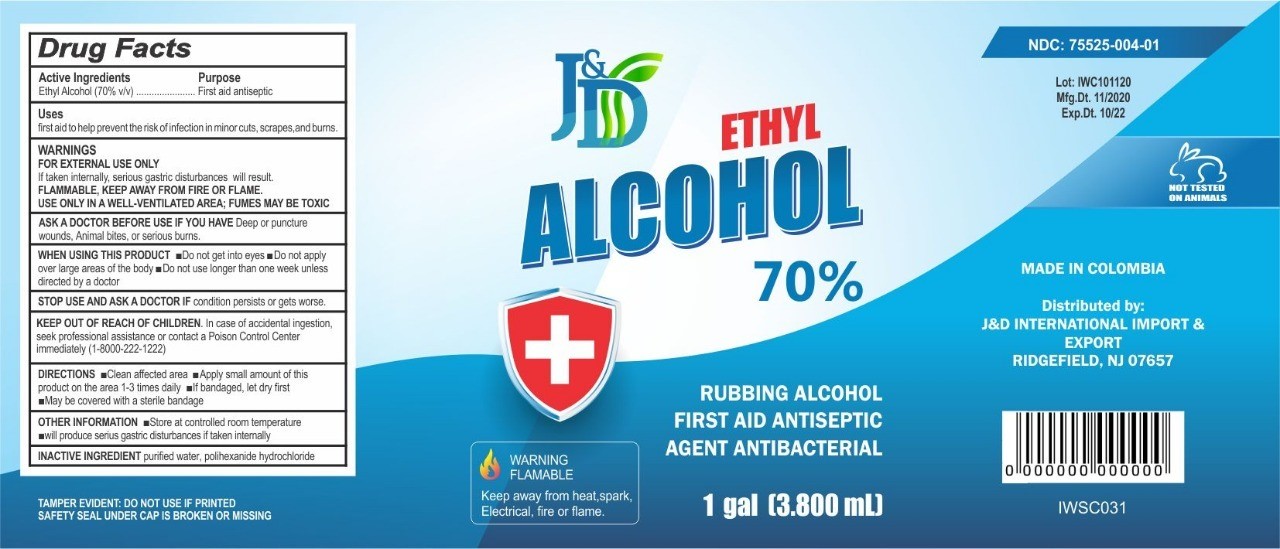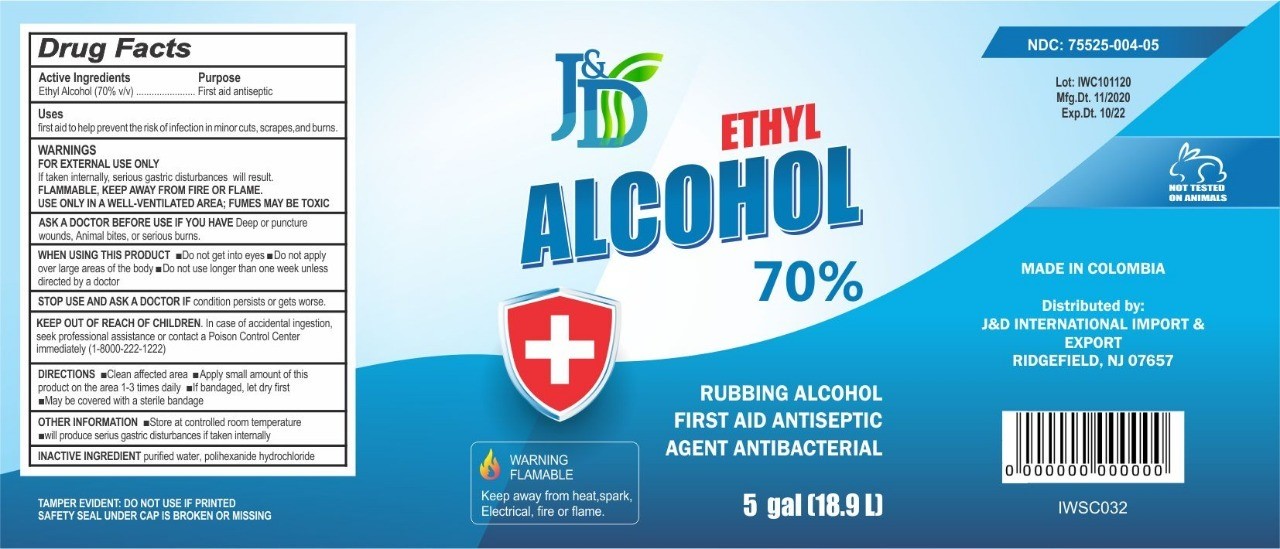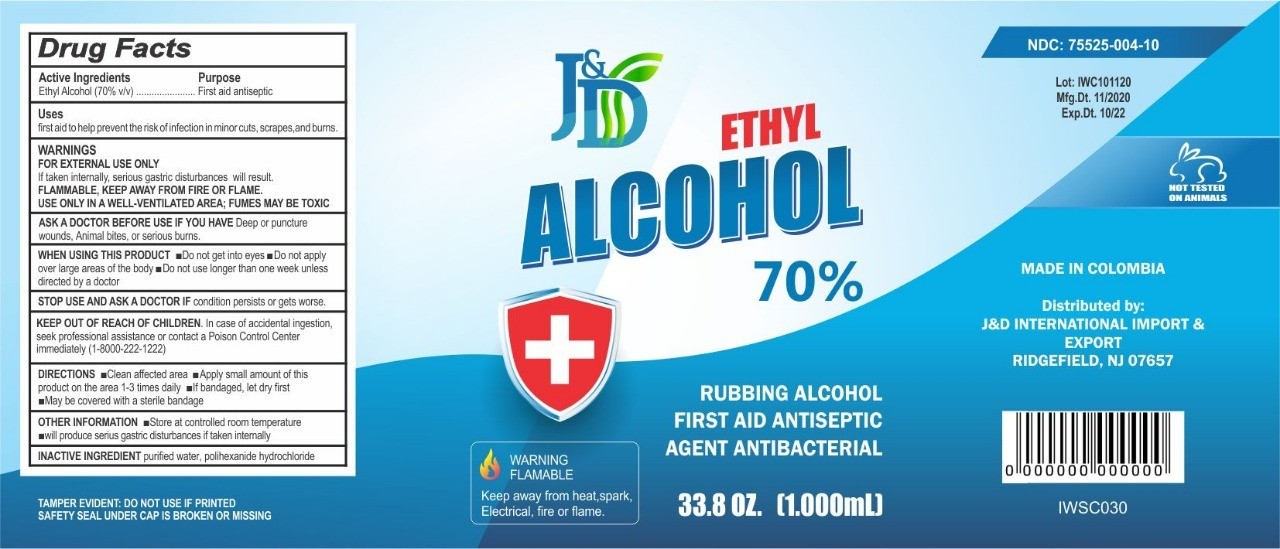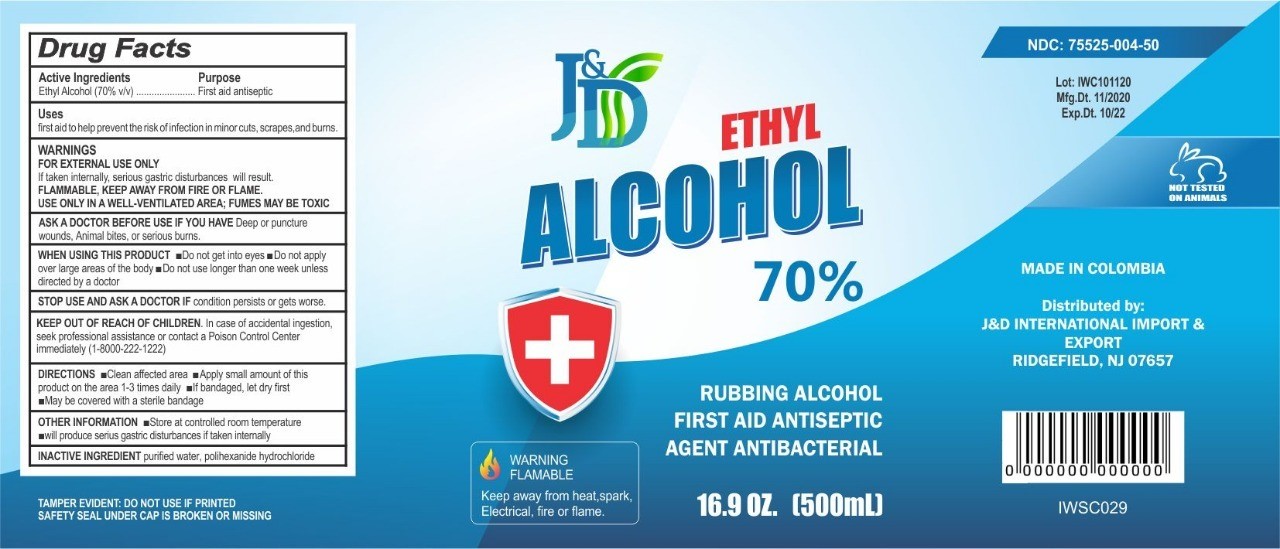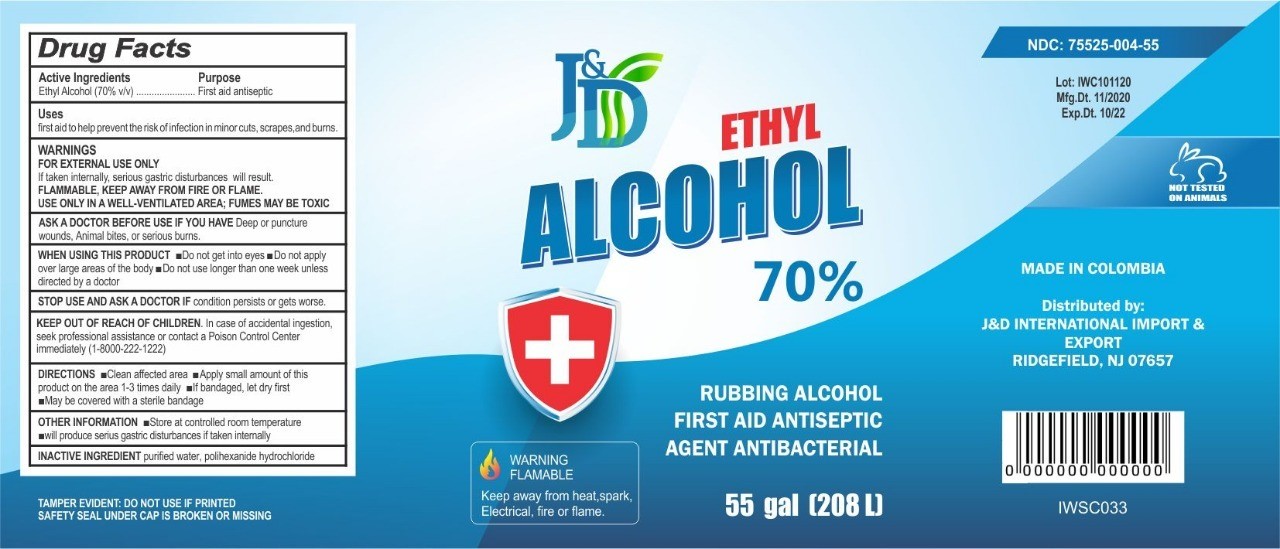 DRUG LABEL: JD Antiseptic Alcohol 70%
NDC: 75525-004 | Form: LIQUID
Manufacturer: IWANNA CORP SAS
Category: otc | Type: HUMAN OTC DRUG LABEL
Date: 20201202

ACTIVE INGREDIENTS: ALCOHOL 72.9 mL/100 mL
INACTIVE INGREDIENTS: POLIHEXANIDE HYDROCHLORIDE 0.1 mL/100 mL; WATER 27 mL/100 mL

ANTISEPTIC ALCOHOL 70%

Rubbing Alcohol

First Aid Antiseptic

Agent Antibacterial

Tamper evident: do not use if printed safety seal under cap is broken or missing

WARNING FLAMMABLE

Keep away from heat, spark, electrical, fire or flame

Active Ingredient(s)

Ethyl Alcohol 70% v/v. Purpose: First Aid Antiseptic

Purpose

First Aid Antiseptic

Use

First Aid to help prevent the risk of infection in minor cuts, scrapes and burns.

Warnings

FOR EXTERNAL USE ONLY

If taken internally, serious gastric disturbances will result

FLAMMABLE, KEEP AWAY FROM FIRE OR FLAME

USE ONLY IN A WELL VENTILATED AREA; FUMES MAY BE TOXIC

ASK A DOCTOR BEFORE USE IF YOU HAVE Deep or puncture wounds, animal bites or serious burns

When using this product

Do not get into the eyes

Do not apply over large areas of the body

Do not use longer than one week unless directed by a Doctor
.

Keep out of reach of children

In case of accidental ingestion, seek professional assistance or contact a Poison Control Center immediately.(1800-222-1222)

Stop Use and ask Doctor

if condition persists or gets worse

Directions

- Clean affected area
- Apply a small amount of this product on the area 1-3 times daily
- If bandaged, let dry first
- May be covered with a sterile bandage

Other information

- Store at controlled room temperature
- Will produce serious gastric disturbances if taken internally

Inactive ingredients

purified water, polihexanide hydrocloride

J&D Ethyl Alcohol 70%- Principal Label

J&D Ethyl Alcohol 70%- 500 ml

500 mL

NDC: 75525-004-50

J&D Ethyl Alcohol 70%- 1000 ml

1000 mL

NDC: 75525-004-10

J&D Ethyl Alcohol 70%- 1 Gal - 3800 ml

1 Gal - 3800 ml

NDC: 75525-004-01

J&D Ethyl Alcohol 70%- 5 Gal- 18.9 L

5 Gal- 18.9 L

NDC: 75525-004-05

J&D Ethyl Alcohol 70%- 55 Gal- 208 L

55 Gal- 208 L

NDC: 75525-004-55